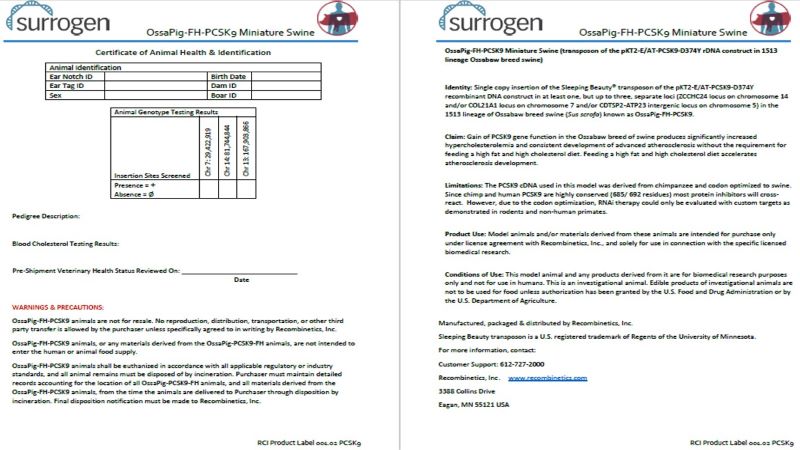 DRUG LABEL: OssaPig-FH-PCSK9 Miniature Swine
NDC: 86086-001 | Form: NOT APPLICABLE
Manufacturer: Recombinetics, Inc.
Category: other | Type: INTENTIONAL ANIMAL GENOMIC ALTERATION LABEL
Date: 20240102

ACTIVE INGREDIENTS: 1.	OSSABOW MINIATURE PIG WITH RDNA CONSTRUCT PCSK-D374Y INSERTED INTO COL21A1 LOCUS ON CHROMOSOME 7 1 [arb'U]/1 [arb'U]; 2.	OSSABOW MINIATURE PIG WITH RDNA CONSTRUCT PCSK-D374Y INSERTED INTO CDTSP2-ATP23 INTERGENIC LOCUS ON CHROMOSOME 5 1 [arb'U]/1 [arb'U]; 3.	OSSABOW MINIATURE PIG WITH RDNA CONSTRUCT PCSK-D374Y INSERTED INTO ZCCHC24 LOCUS ON CHROMOSOME 14 1 [arb'U]/1 [arb'U]

STATEMENT OF IDENTITY

Identity: Single copy insertion of the Sleeping Beauty® transposon of the pKT2-E/AT-PCSK9-D374Y recombinant DNA construct in at least one, but up to three, separate loci (ZCCHC24 locus on chromosome 14 and/or COL21A1 locus on chromosome 7 and/or CDTSP2-ATP23 intergenic locus on chromosome 5) in the 1513 lineage of Ossabaw breed swine (Sus scrofa) known as OssaPig-FH-PCSK9.

HEALTH CLAIM

Claim: Gain of PCSK9 gene function in the Ossabaw breed of swine produces significantly increased hypercholesterolemia and consistent development of advanced atherosclerosis without the requirement for feeding a high fat and high cholesterol diet. Feeding a high fat and high cholesterol diet accelerates atherosclerosis development.

CONTRAINDICATIONS

Limitations: The PCSK9 cDNA used in this model was derived from chimpanzee and codon optimized to swine. Since chimp and human PCSK9 are highly conserved (685/ 692 residues) most protein inhibitors will cross-react. However, due to the codon optimization, RNAi therapy could only be evaluated with custom targets as demonstrated in rodents and non-human primates.

INDICATIONS AND USAGE

Product Use: Model animals and/or materials derived from these animals are intended for purchase only under license agreement with Recombinetics, Inc., and solely for use in connection with the specific licensed biomedical research.

INDICATIONS AND USAGE

Conditions of Use: This model animal and any products derived from it are for biomedical research purposes only and not for use in humans. This is an investigational animal. Edible products of investigational animals are not to be used for food unless authorization has been granted by the U.S. Food and Drug Administration or by the U.S. Department of Agriculture.

REFERENCES

Manufactured, packaged & distributed by Recombinetics, Inc., under U.S. Veterinary Master File V-006248. Sleeping Beauty transposon is a U.S. registered trademark of Regents of the University of Minnesota.

WARNINGS AND PRECAUTIONS

Caution. This intentionally genetically altered animal and any products derived from it are for biomedical research purposes only and are not for use in humans or as human or animal food.

OssaPig-FH-PCSK9 animals are not for resale. No reproduction, distribution, transportation, or other third party transfer is allowed by the purchaser unless specifically agreed to in writing by Recombinetics, Inc.
OssaPig-FH-PCSK9 animals, or any materials derived from the OssaPig-PCSK9-FH animals, are not intended to enter the human or animal food supply.
OssaPig-FH-PCSK9 animals shall be euthanized in accordance with all applicable regulatory or industry standards, and all animal remains must be disposed of by incineration. Purchaser must maintain detailed records accounting for the location of all OssaPig-PCSK9-FH animals, and all materials derived from the OssaPig-FH-PCSK9 animals, from the time the animals are delivered to Purchaser through disposition by incineration. Final disposition notification must be made to Recombinetics, Inc.